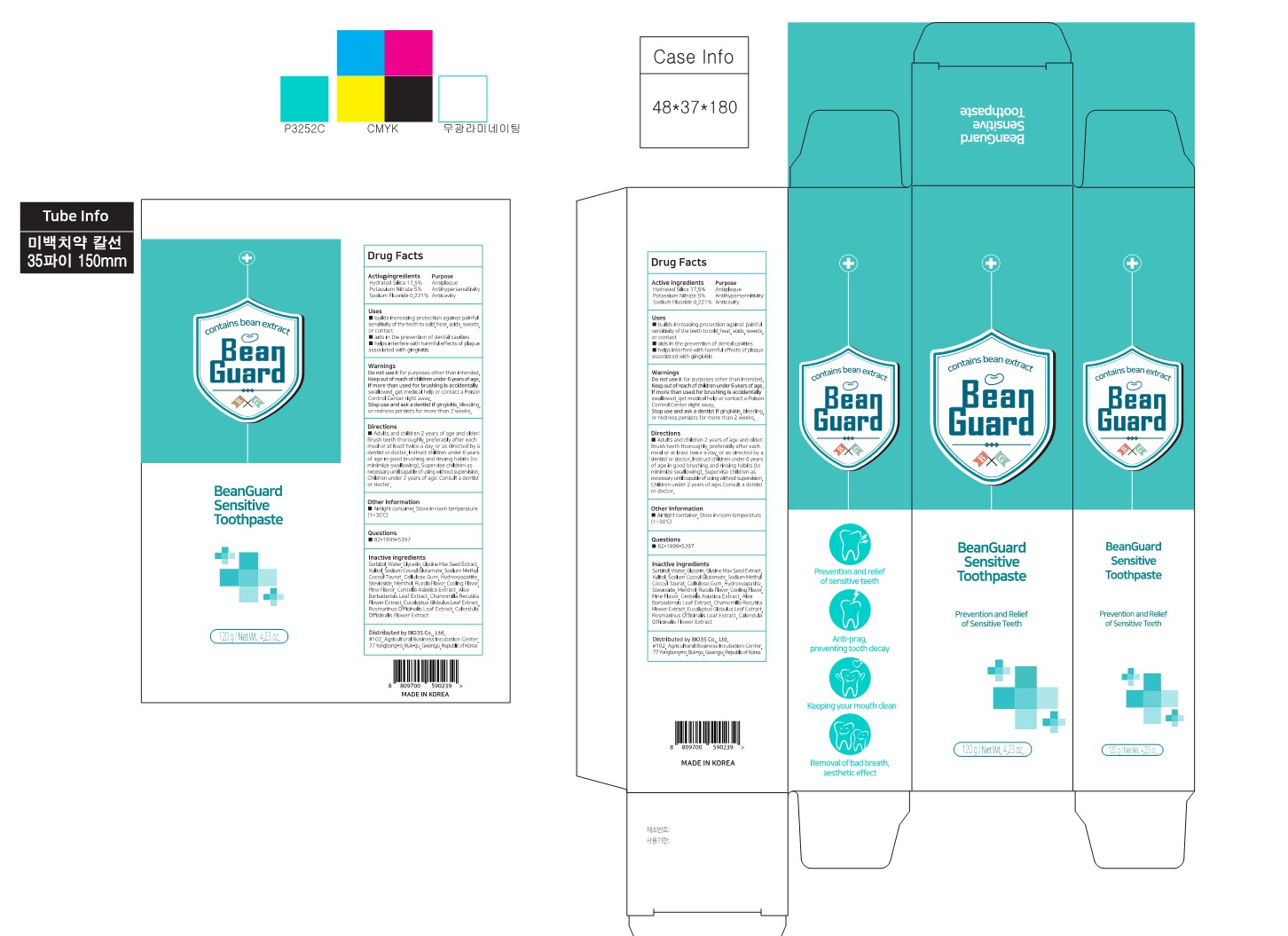 DRUG LABEL: BeanGuard Sensitivetoothpaste
NDC: 77935-401 | Form: PASTE, DENTIFRICE
Manufacturer: BIO3S Co.,Ltd.
Category: otc | Type: HUMAN OTC DRUG LABEL
Date: 20221222

ACTIVE INGREDIENTS: POTASSIUM NITRATE 5 g/100 mL; SODIUM FLUORIDE 0.221 g/100 mL; HYDRATED SILICA 17.5 g/100 mL
INACTIVE INGREDIENTS: GLYCERIN; SODIUM COCOYL GLUTAMATE; MARITIME PINE; STEVIOSIDE; MENTHOL; SOYBEAN; WATER; XYLITOL; SODIUM METHYL COCOYL TAURATE; TRIBASIC CALCIUM PHOSPHATE; SORBITOL; EUCALYPTOL; CHAMOMILE; EUCALYPTUS GLOBULUS LEAF; ROSEMARY; CALENDULA OFFICINALIS FLOWER; BRASSICA OLERACEA WHOLE; CARBOXYMETHYLCELLULOSE SODIUM, UNSPECIFIED FORM; CENTELLA ASIATICA TRITERPENOIDS; ALOE VERA LEAF

77935-401 BeanGuard Sensitive toothpaste

Active ingredients

Hydrated Silica 17.5%
Potassium Nitrate 5%
Sodium Fluoride 0.221%

Purposes

Hydrated Silica 17.5% Antiplaque
Potassium Nitrate 5% Antihypersensitivity
Sodium Fluoride 0.221% Anticavity

Uses

■ builds increasing protection against painful sensitivity of the teeth to cold, heat, acids, sweets, or contact
■ aids in the prevention of dental cavities
■ helps interfere with harmful effects of plaque associated with gingivitis

Warnings

Do not use it for purposes other than intended.
Keep out of reach of children under 6 years of age.
If more than used for brushing is accidentally swallowed, get medical help or contact a Poison
Control Center right away.
Stop use and ask a dentist if gingivitis, bleeding, or redness persists for more than 2 weeks.

Warnings

If more than used for brushing is accidentally swallowed, get medical help or contact a Poison Control Center right away.

Warnings

Stop use and ask a dentist if gingivitis, bleeding, or redness persists for more than 2 weeks.

Warnings

Keep out of reach of children under 6 years of age.

Warnings

Do not use it for purposes other than intended.

Directions

■ Adults and children 2 years of age and older:

Brush teeth thoroughly, preferably after each meal or at least twice a day, or as directed by a dentist or doctor.

Instruct children under 6 years of age in good brushing and rinsing habits (to minimize swallowing).

Supervise children as necessary until capable of using without supervision.
Children under 2 years of age: Consult a dentist or doctor.

Inactive ingredients

Sorbitol, Water; Glycerin, Glycine Max Seed Extract, Xylitol, Sodium Cocoyl Glutamate, Sodium Methyl Cocoyl Taurat, Cellulose Gum, Hydroxyapatite, Stevioside, Menthol, Rucola Flavor, Cooling Flavor, Pine Flavor, Centella Asiatics Extract, Aloe Barbadensis Leaf Extract, Chamomilla Recutita Flower Extract, Eucalyptus Globulus Leaf Extract, Rosmarinus Officinalis Leaf Extract, Calendula Officinalis Flower Extract